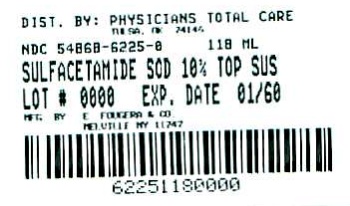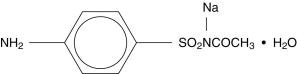 DRUG LABEL: Sulfacetamide Sodium
NDC: 54868-6225 | Form: SUSPENSION
Manufacturer: Physicians Total Care, Inc.
Category: prescription | Type: HUMAN PRESCRIPTION DRUG LABEL
Date: 20090901

ACTIVE INGREDIENTS: SULFACETAMIDE SODIUM 100 mg/1 mL
INACTIVE INGREDIENTS: WATER; SODIUM CHLORIDE; SODIUM METABISULFITE; EDETATE DISODIUM; XANTHAN GUM; PROPYLENE GLYCOL; METHYLPARABEN

SULFACETAMIDE SODIUM
TOPICAL SUSPENSION USP, 10%

Rx only

DESCRIPTION

Each mL of Sulfacetamide Sodium Topical Suspension USP, 10% contains 100 mg of sulfacetamide sodium in a vehicle consisting of purified water, propylene glycol, lauramide DEA (and) diethanolamine, polyethylene glycol 400 monolaurate, hydroxyethyl cellulose, sodium chloride, sodium metabisulfite, methylparaben, xanthan gum, EDTA and simethicone. Sulfacetamide sodium is a sulfonamide with antibacterial activity. Chemically sulfacetamide sodium is N' -[(4-aminophenyl) sulfonyl]-acetamide, monosodium salt, monohydrate. The structural formula is:

CLINICAL PHARMACOLOGY

The most widely accepted mechanism of action of sulfonamides is the Woods-Fildes theory, based on sulfonamides acting as a competitive inhibitor of para-aminobenzoic acid (PABA) utilization, an essential component for bacterial growth. While absorption through intact skin in humans has not been determined, in vitro studies with human cadaver skin indicated a percutaneous absorption of about 4%. Sulfacetamide sodium is readily absorbed from the gastrointestinal tract when taken orally and excreted in the urine largely unchanged. The biological half-life has been reported to be between 7 to 13 hours.

INDICATIONS AND USAGE

Sulfacetamide Sodium Topical Suspension USP, 10% is indicated in the topical treatment of acne vulgaris.

CONTRAINDICATIONS

Sulfacetamide Sodium Topical Suspension USP, 10% is contraindicated for use by patients having a known hypersensitivity to sulfonamides or any other component of this preparation (see WARNINGS section).

WARNINGS

Fatalities have occurred, although rarely, due to severe reactions to sulfonamides including Stevens-Johnson syndrome, toxic epidermal necrolysis, fulminant hepatic necrosis, agranulocytosis, aplastic anemia, and other blood dyscrasias. Hypersensitivity reactions may occur when a sulfonamide is readministered, irrespective of the route of administration. Sensitivity reactions have been reported in individuals with no prior history of sulfonamide hypersensitivity. At the first sign of hypersensitivity, skin rash or other reactions, discontinue use of this preparation (see ADVERSE REACTIONS section).

Sulfacetamide Sodium Topical Suspension USP, 10% contains sodium metabisulfite, a sulfite that may cause allergic-type reactions including anaphylactic symptoms and life threatening or less severe asthmatic episodes in certain susceptible people. The overall prevalence of sulfite sensitivity in the general population is unknown and probably low. Sulfite sensitivity is seen more frequently in asthmatic than non-asthmatic people (see CONTRAINDICATIONS section).

PRECAUTIONS

GENERAL PRECAUTIONS

General: For external use only. Keep away from eyes. If irritation develops, use of the product should be discontinued and appropriate therapy instituted. Patients should be carefully observed for possible local irritation or sensitization during long-term therapy. Hypersensitivity reactions may occur when a sulfonamide is readministered irrespective of the route of administration, and cross-sensitivity between different sulfonamides may occur. Sulfacetamide sodium can cause reddening and scaling of the skin. Particular caution should be employed if areas of involved skin to be treated are denuded or abraded.

Keep out of reach of children.

CARCINOGENESIS AND MUTAGENESIS AND IMPAIRMENT OF FERTILITY

Carcinogenesis, Mutagenesis and Impairment of Fertility: Long term studies in animals have not been performed to evaluate carcinogenic potential.

PREGNANCY

Pregnancy- Category C: Animal reproduction studies have not been conducted with Sulfacetamide Sodium Topical Suspension USP, 10%. It is also not known whether Sulfacetamide Sodium Topical Suspension USP, 10% can cause fetal harm when administered to a pregnant woman or can affect reproduction capacity. Sulfacetamide Sodium Topical Suspension USP, 10% should be given to a pregnant woman only if clearly needed.

Kernicterus may occur in the newborn as a result of treatment of a pregnant woman at term with orally administered sulfonamide. There are no adequate and well controlled studies of Sulfacetamide Sodium Topical Suspension USP, 10% in pregnant women, and it is not known whether topically applied sulfonamides can cause fetal harm when administered to a pregnant woman.

NURSING MOTHERS

Nursing Mothers: It is not known whether sulfacetamide sodium is excreted in the human milk following topical use of Sulfacetamide Sodium Topical Suspension USP, 10%. Systemically administered sulfonamides are capable of producing kernicterus in the infants of lactating women. Small amounts of orally administered sulfonamides have been reported to be eliminated in human milk. Because many drugs are excreted in human milk, caution should be exercised in prescribing for nursing mothers.

PEDIATRIC USE

Pediatric Use: Safety and effectiveness in pediatric patients under the age of 12 have not been established.

ADVERSE REACTIONS

In controlled clinical trials for the management of acne vulgaris, the occurrence of adverse reactions associated with the use of Sulfacetamide Sodium Topical Suspension USP, 10% was infrequent and restricted to local events. The total incidence of adverse reactions reported in these studies was less than 2%. Only one of 105 patients treated with Sulfacetamide Sodium Topical Suspension USP, 10% had local adverse reactions of erythema, itching and edema. It has been reported that sulfacetamide sodium may cause local irritation, stinging and burning. While the irritation may be transient, occasionally, the use of the medication has to be discontinued.

DOSAGE AND ADMINISTRATION

Apply a thin film to affected areas twice daily.

HOW SUPPLIED

Sulfacetamide Sodium Topical Suspension USP, 10%, is supplied in

118 mL bottles NDC 54868-6225-0

Store at controlled room temperature 20°-25°C (68°-77°F) [see USP].

Shake well before using. Keep tightly closed.

E. FOUGERA & CO.
A division of Nycomed US Inc.
MELVILLE, NEW YORK 11747

I2382A
R11/07
#280

Relabeling of "Additional" barcode label by:
Physicians Total Care, Inc.
Tulsa, OK 74146

PACKAGE LABEL – PRINCIPAL DISPLAY PANEL – 118 mL (4 fl oz)

SULFACETAMIDE

SODIUM TOPICAL

SUSPENSION USP, 10%

USUAL DOSAGE: Shake well before using. Apply a thin film to the affected areas twice daily. See package insert for full prescribing information.

WARNING: Keep away from eyes. For external use only. Keep out of reach of children.

Store at Controlled Room Temperature 20°-25°C (68°-77°F) [see USP]. Keep tightly closed.

Each mL of Sulfacetamide Sodium Topical Suspension USP, 10% contains 100 mg of sulfacetamide sodium in a vehicle consisting of purified water, propylene glycol, lauramide DEA (and) diethanolamine, polyethylene glycol 400 monolaurate, hydroxyethyl cellulose, sodium chloride, sodium metabisulfite, methylparaben, xanthan gum, EDTA and simethicone.

PACKAGE LABEL

SULFACETAMIDE

SODIUM TOPICAL

SUSPENSION

USP, 10%

Rx only

118 mL (4 fl oz)